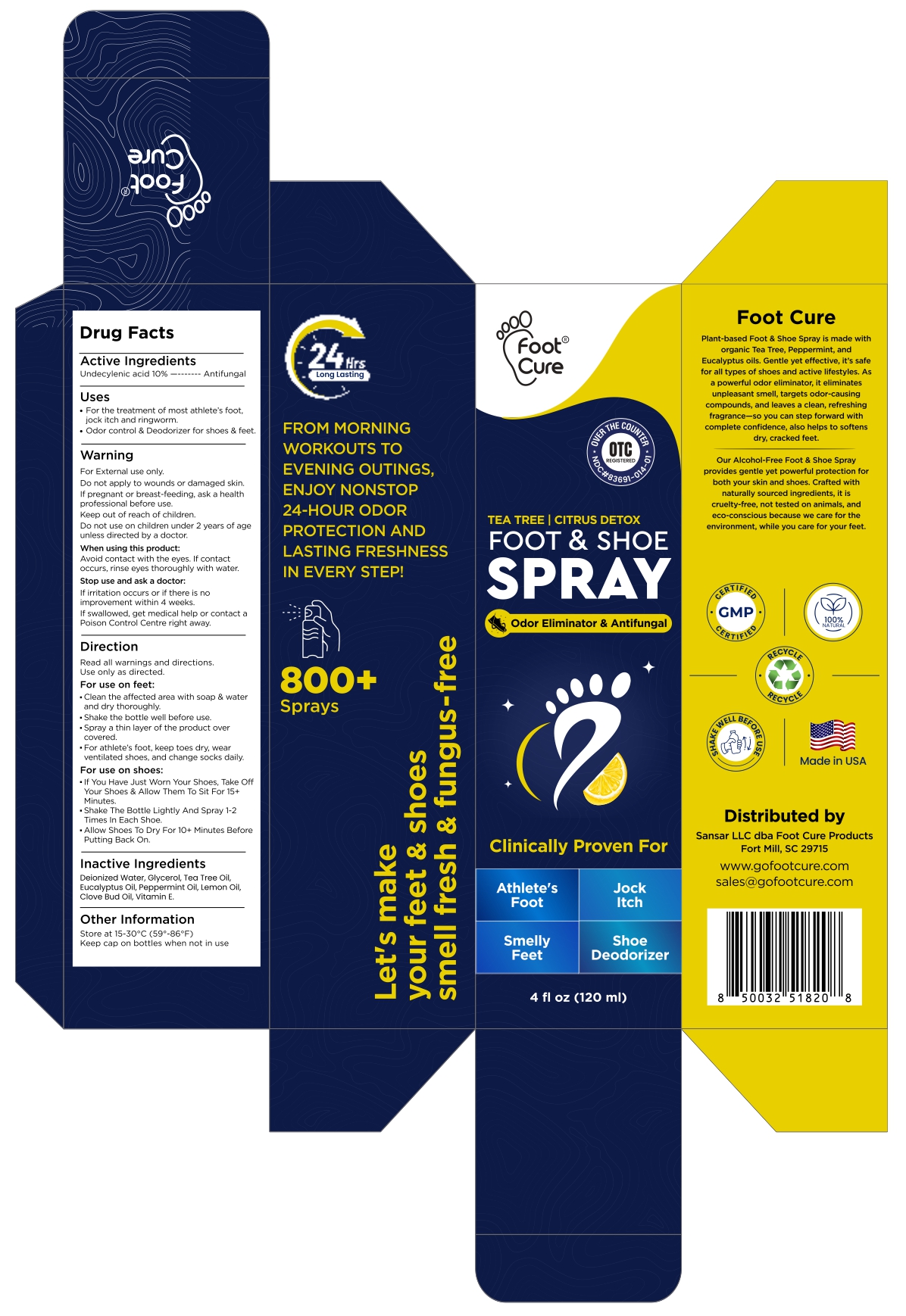 DRUG LABEL: Citrus Detox Foot and Shoe Antifungal
NDC: 83691-014 | Form: SPRAY
Manufacturer: SANSAR, LLC
Category: otc | Type: HUMAN OTC DRUG LABEL
Date: 20251115

ACTIVE INGREDIENTS: UNDECYLENIC ACID 10 g/100 mL
INACTIVE INGREDIENTS: WATER; GLYCERIN; TEA TREE OIL; EUCALYPTUS OIL; PEPPERMINT OIL; LEMON OIL, COLD PRESSED; CLOVE OIL; .ALPHA.-TOCOPHEROL

Citrus Detox-Foot and Shoe Antifungal Spray

Active Ingredient

Undecylenic acid 10%

Purpose

Antifungal

Uses

• For the treatment of most athlete's foot, jock Itch and ringworm.
• Odor control & Deodorizer for shoes & feet.

Warnings

For External use only.

Do not apply to wounds or damaged skin.

PREGNANCY OR BREAST FEEDING

lf pregnant or breast-feeding, ask a health professional before use.

Keep out of reach of children.

Do not use on children under 2 years of age unless directed by a doctor.

When using this product: Avoid contact with the eyes. If contact occurs, rinse eyes thoroughly with water.

Stop use and ask a doctor: If irritation occurs or if there is no improvement within 4 weeks.

If swallowed, get medical help or contact a Poison control centre right away.

Direction

Read all warnings and directions. Use only as directed.

For use on feet:

• Clean the affected area with soap & water and dry thoroughly.
• Shake the bottle well before use.
• Spray a thin layer of the product over covered.
• For athlete's foot, keep toes dry, wear ventilated shoes,and change socks daily.

For use on shoes:

• If you have just worn your Shoes, Take Off your Shoes & Allow them to sit For 15+ Minutes.
• Shake the Bottle lightly and Spray 1-2 Times In each Shoe.
• Allow Shoes to Dry for 10+ Minutes Before Putting Back On.

Inactive Ingredients

Deionized Water, Glycerol, Tea Tree Oil, Eucalyptus Oil, Peppermint Oil, Lemon Oil, Clove Bud Oil, Vltamin E.

Other Information

Store at 15-30°C(59°-86°F)
Keep cap on bottles when not in use